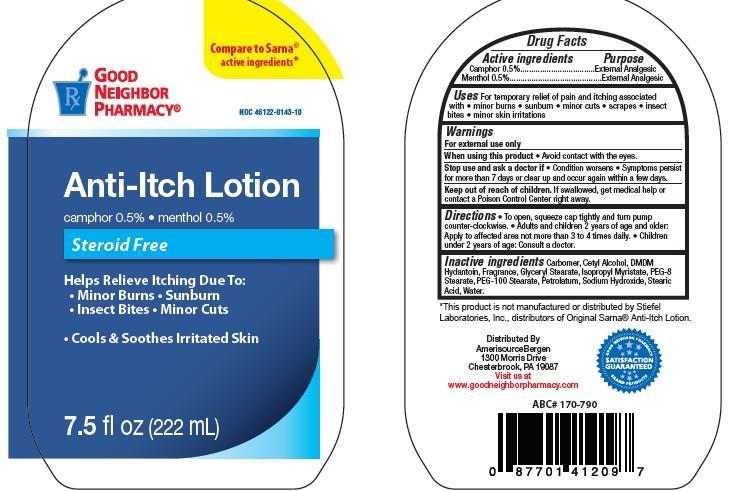 DRUG LABEL: Good Neighbor Pharmacy Anti-Itch
NDC: 46122-143 | Form: LOTION
Manufacturer: AmerisourceBergen Drug Corporation
Category: otc | Type: HUMAN OTC DRUG LABEL
Date: 20151112

ACTIVE INGREDIENTS: CAMPHOR (NATURAL) .5 g/100 mL; MENTHOL .5 g/100 mL
INACTIVE INGREDIENTS: CARBOMER 934; CETYL ALCOHOL; DMDM HYDANTOIN; GLYCERYL STEARATE SE; ISOPROPYL MYRISTATE; PEG-8 STEARATE; PEG-100 STEARATE; PETROLATUM; SODIUM HYDROXIDE; STEARIC ACID; WATER

Good Neighbor Pharmacy Anti-Itch

Active ingredients

Camphor 0.5%

Menthol 0.5%

Purpose

External Analgesic

Uses

For temporary relief of pain and itching associated with • minor burns • sunburn • minor cuts • scra pes • insect

bites • minor skin irritations

Warnings

For external use only

When using this product

Avoid contact with the eyes.

Stop use and ask a doctor if

Condition worsens • Symptoms persist for more than 7 days or clear up and occur again within a few days.

Keep out of reach of children.

If swallowed, get medical help or

contact a Poison Control Center right away.

Directions

To open, squeeze cap tightly and turn pump counter-clockwise. • Adults and children 2 years of age and older:

Apply to affected area not more than 3 to 4 times daily. • Children under 2 years of age: Consult a doctor.

Inactive ingredients

Carbomer, Cetyl Alcohol, DMDMHydantoin, Fragrance, Glyceryl Stearate, Isopropyl Myristate, PEG-8

Stearate, PEG-100 Stearate, Petrolatum, Sodium Hydroxide, Stearic Acid, Water.

*This product is not manufactured or distributed by Stiefel

Laboratories, Inc., distributors of Original Sarna® Anti-Itch Lotion.

Distributed By

AmerisourceBergen

1300 Morris Drive

Chesterbrook, PA 19087

Visit us at

www.goodneighborpharmacy.com